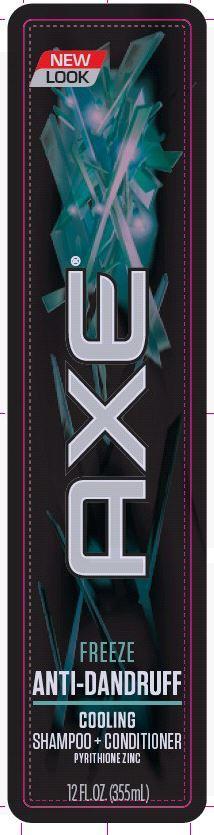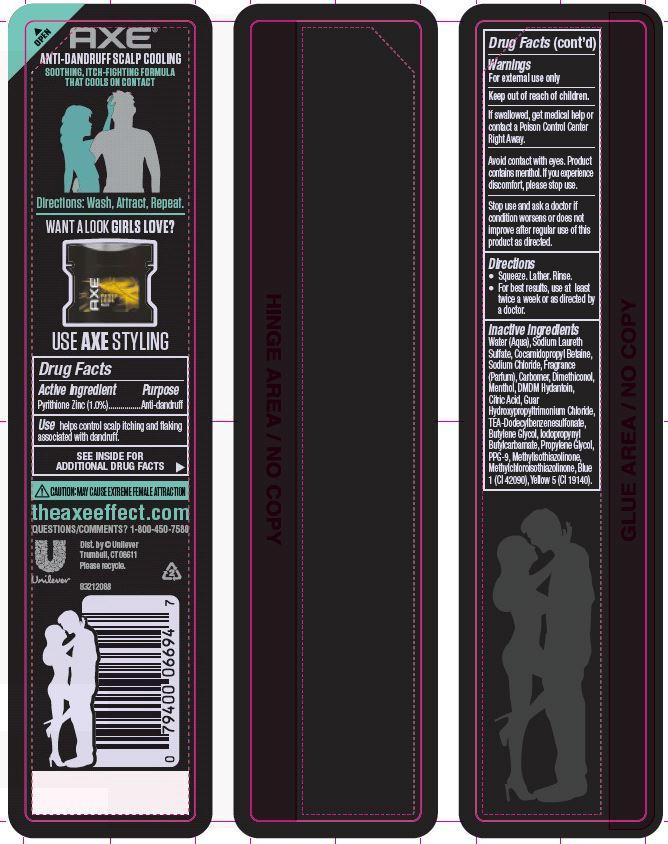 DRUG LABEL: Axe
NDC: 64942-1357 | Form: SHAMPOO
Manufacturer: Conopco Inc. d/b/a Unilever
Category: otc | Type: HUMAN OTC DRUG LABEL
Date: 20140424

ACTIVE INGREDIENTS: Pyrithione Zinc 1 g/100 mL
INACTIVE INGREDIENTS: WATER; SODIUM LAURETH SULFATE; COCAMIDOPROPYL BETAINE; SODIUM CHLORIDE; CARBOMER HOMOPOLYMER TYPE C; BUTYLENE GLYCOL; MENTHOL; DMDM HYDANTOIN; GUAR HYDROXYPROPYLTRIMONIUM CHLORIDE (1.7 SUBSTITUENTS PER SACCHARIDE); TRIETHANOLAMINE DODECYLBENZENESULFONATE; CITRIC ACID MONOHYDRATE; IODOPROPYNYL BUTYLCARBAMATE; PROPYLENE GLYCOL; METHYLCHLOROISOTHIAZOLINONE; METHYLISOTHIAZOLINONE; PPG-9; FD&C BLUE NO. 1; FD&C YELLOW NO. 5

Axe Freeze Anti-Dandruff shampoo+conditioner

Active Ingredient
Pyrithione Zinc (1.0%)

Purpose

Anti-dandruff

INDICATIONS AND USAGE

Use helps control scalp itching and flaking associated with dandruff.

Warnings
For external use only

Keep out of reach of children.

If swallowed, get medical help or contact a Poison Control Center Right Away.

STOP USE

Avoid contact with eyes. Product contains menthol. If you experience discomfort, please stop use.

Stop use and ask a doctor if condition worsens or does not improve after regular use of this product as directed.

DOSAGE AND ADMINISTRATION

Direction

· Squeeze. Lather. Rinse
· For best results, use at least twice a week or as directed by a doctor.

Inactive ingredients
Water (Aqua), Sodium Laureth Sulfate, Cocamidopropyl Betaine, Sodium Chloride, Fragrance (Parfum), Carbomer, Dimethiconol, Menthol, DMDM Hydantoin, Citric Acid, Guar Hydroxypropyltrimonium Chloride, TEA-Dodecylbenzenesulfonate, Butylene Glycol, Iodopropynyl Butylcarbamate, Propylene Glycol, PPG-9, Methylisothiazolinone, Methylchloroisothiazolinone, Blue 1 (CI 42090), Yellow 5 (CI 19140).

QUESTIONS

theaxeeffect.com
QUESTIONS/COMMENTS?
1-800-450-7580